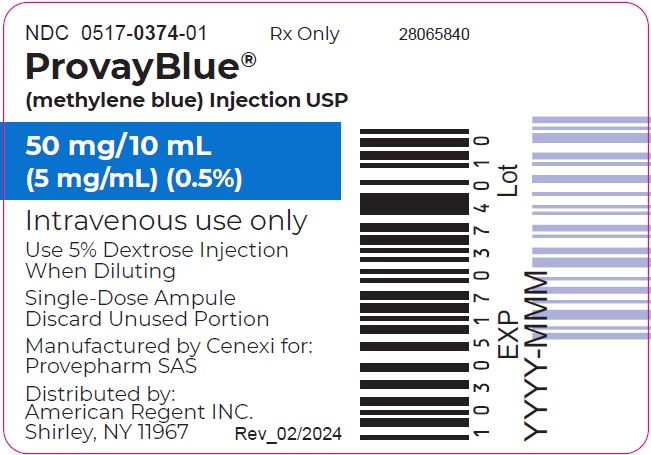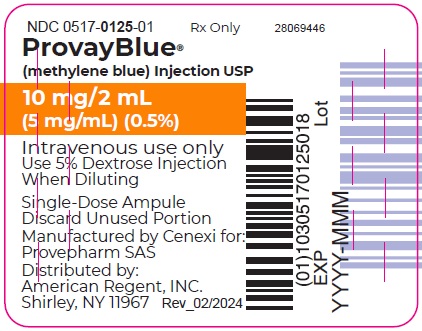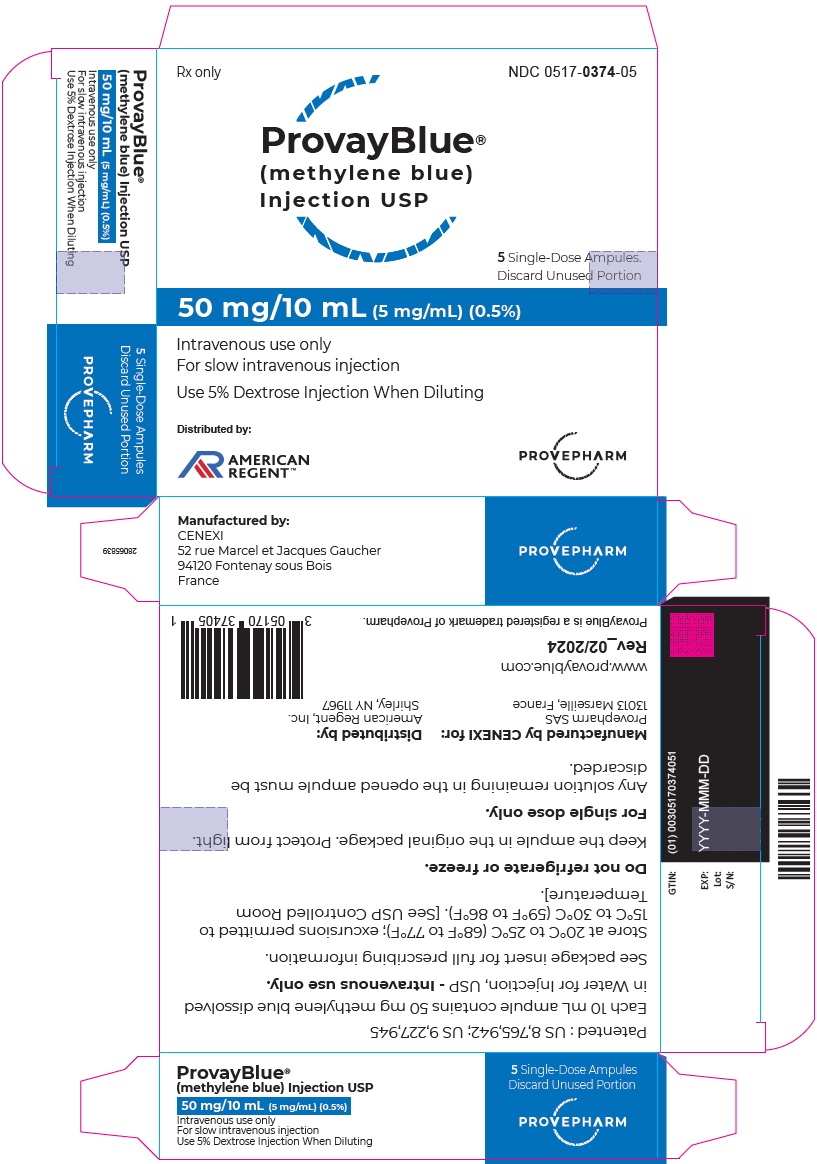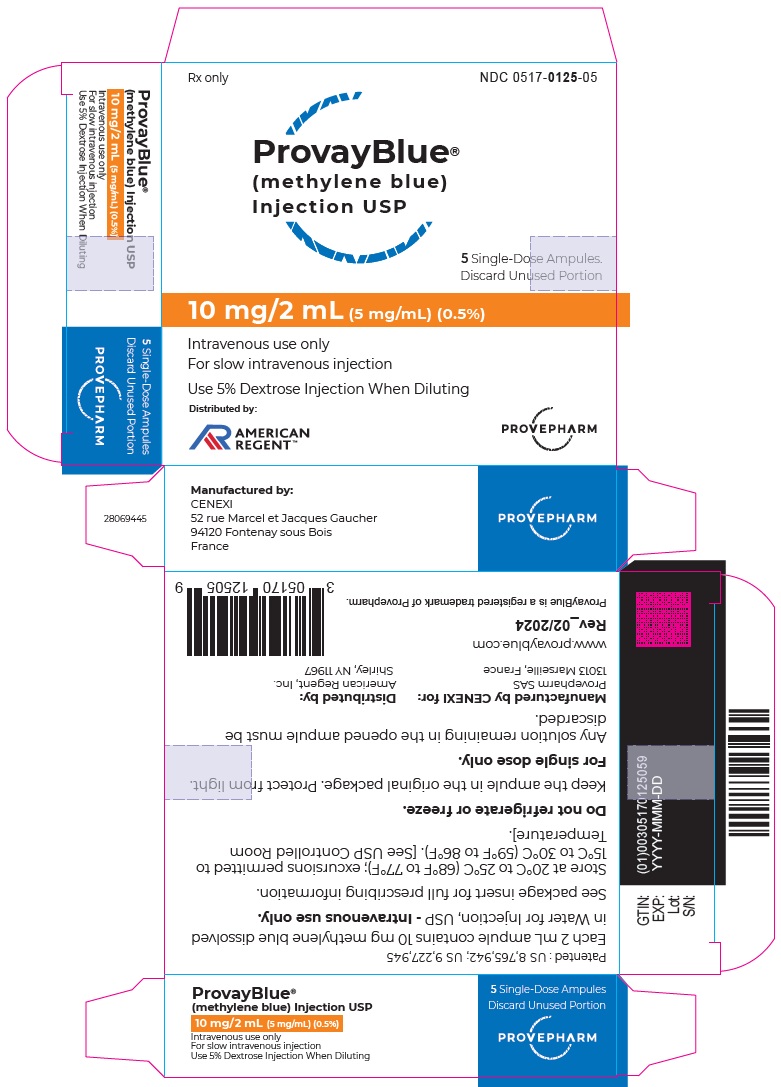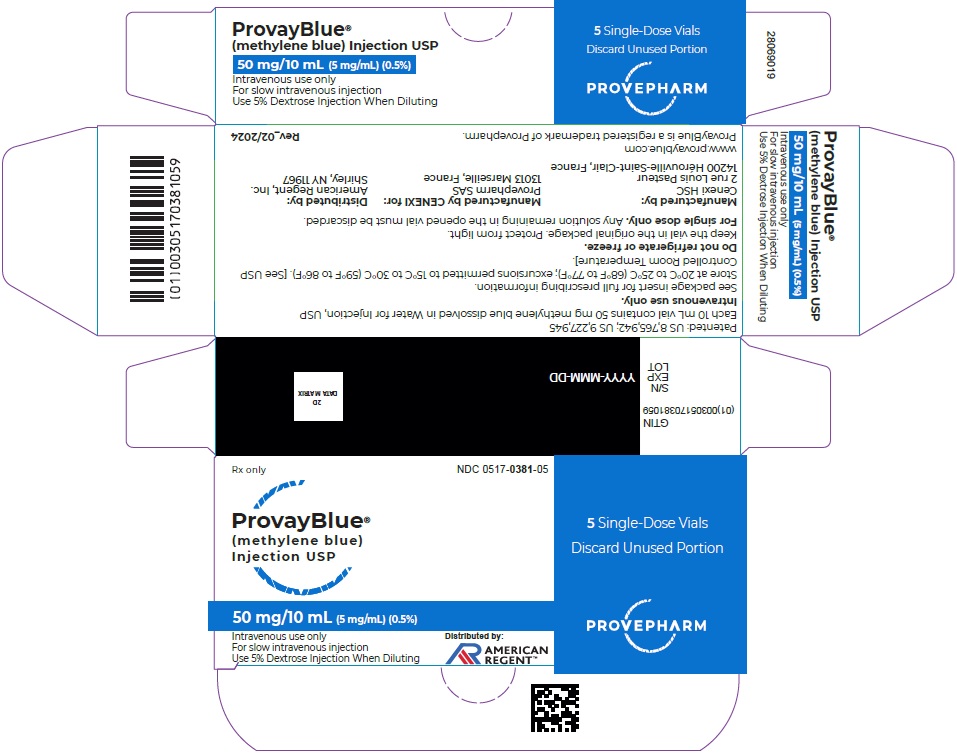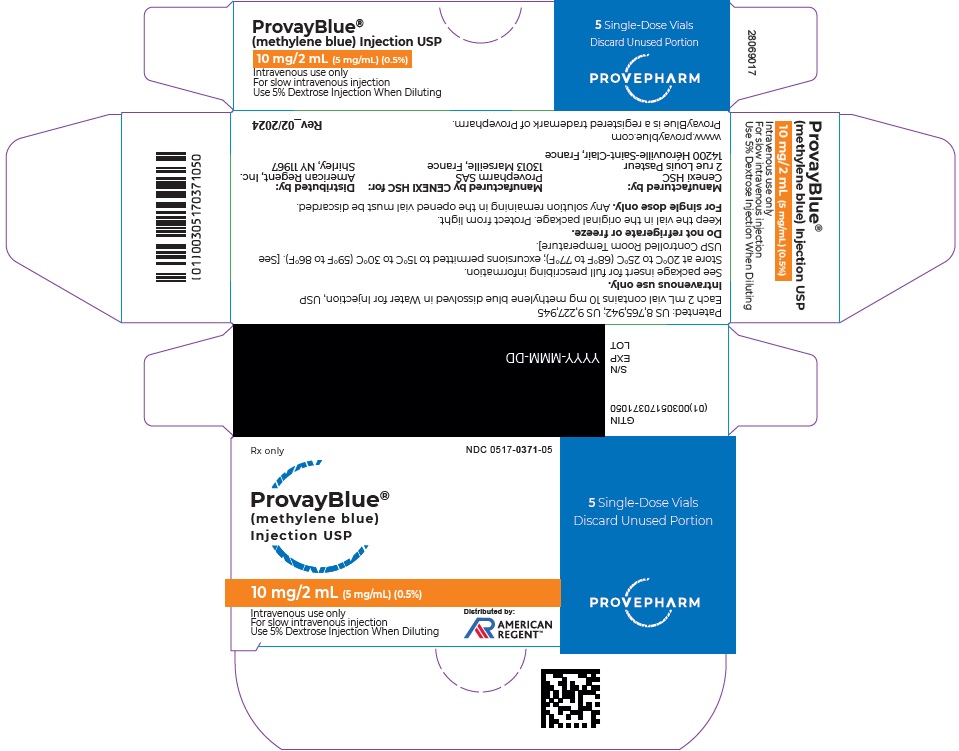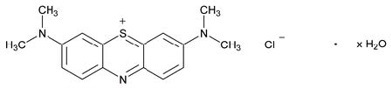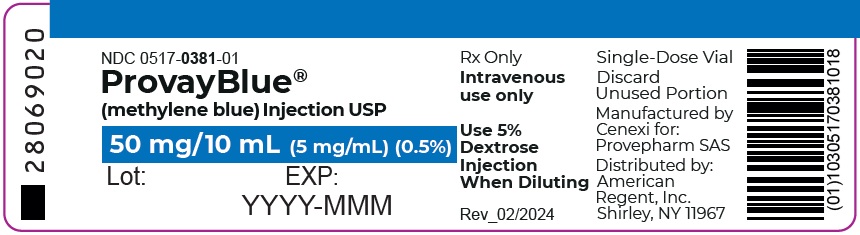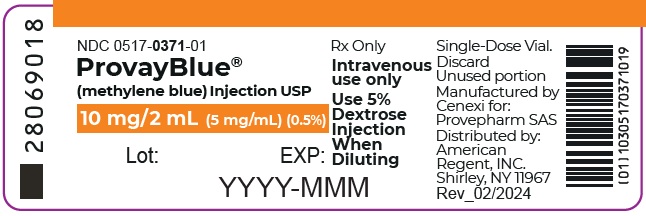 DRUG LABEL: PROVAYBLUE
NDC: 0517-0374 | Form: INJECTION
Manufacturer: American Regent, Inc.
Category: prescription | Type: HUMAN PRESCRIPTION DRUG LABEL
Date: 20250528

ACTIVE INGREDIENTS: METHYLENE BLUE
 5 mg/1 mL
INACTIVE INGREDIENTS: WATER

HIGHLIGHTS OF PRESCRIBING INFORMATION

These highlights do not include all the information needed to use (PROVAYBLUE) safely and effectively. See full prescribing information for (PROVAYBLUE).
PROVAYBLUE® (methylene blue) injection, USP for intravenous use
Initial U.S. Approval: 2016

WARNING: SEROTONIN SYNDROME WITH CONCOMITANT USE OF SEROTONERGIC DRUGS AND OPIOIDS

See full prescribing information for complete boxed warning.

PROVAYBLUE may cause serious or fatal serotonergic syndrome when used in combination with serotonergic drugs and opioids. Avoid concomitant use of PROVAYBLUE with selective serotonin reuptake inhibitors (SSRIs), serotonin norepinephrine reuptake inhibitors (SNRIs), monoamine oxidase inhibitors (MAOIs) and opioids. (5.1, 7.1)

RECENT MAJOR CHANGES

Boxed Warning 11/2023
Indications and Usage (1) 01/2024
Warnings and Precautions (5) 11/2023

1 INDICATIONS AND USAGE

PROVAYBLUE (methylene blue) is an oxidation-reduction agent indicated for the treatment of pediatric and adult patients with acquired methemoglobinemia.

2 DOSAGE AND ADMINISTRATION

- Administer 1 mg/kg intravenously over 5-30 minutes. (2.1)
- If methemoglobin level remains above 30% or if clinical symptoms persist, give a repeat dose of up to 1 mg/kg one hour after the first dose. (2.1)
- Administer a single dose of 1 mg/kg in patients with moderate or severe renal impairment. (2.2)

3 DOSAGE FORMS AND STRENGTHS

- 50 mg/10 mL (5 mg/mL) single-dose ampule. (3)
- 10 mg/2 mL (5 mg/mL) single-dose ampule. (3)
- 50 mg/10 mL (5 mg/mL) single-dose vial. (3)
- 10 mg/2 mL (5 mg/mL) single-dose vial. (3)

4 CONTRAINDICATIONS

PROVAYBLUE is contraindicated in the following conditions (4):

- Severe hypersensitivity to methylene blue
- Patients with glucose-6-phosphate dehydrogenase deficiency (G6PD) due to the risk of hemolytic anemia

5 WARNINGS AND PRECAUTIONS

- Hypersensitivity: If severe or life threatening allergic reaction occurs, discontinue PROVAYBLUE, treat the allergic reaction, and monitor until signs and symptoms resolve (5.2)
- Lack of Effectiveness: Consider alternative treatments if there is no resolution of methemoglobinemia after 2 doses (2.1, 5.3)
- Hemolytic Anemia: Discontinue PROVAYBLUE and transfuse (5.4)
- Interference with In-Vivo Monitoring Devices: Use methods other than pulse oximetry to assess oxygen saturation (5.5)
- Effects on Ability to Drive and Operate Machinery: Advise patients to refrain from these activities until neurologic and visual symptoms have resolved (5.6)

6 ADVERSE REACTIONS

The most commonly reported adverse reactions (>2%) included headache, hypokalemia, diarrhea, hypomagnesemia, myoclonus, nausea, and seizure-like phenomena. (6.1)

To report SUSPECTED ADVERSE REACTIONS, contact American Regent at 1-800-734-9236, FDA at 1-800-FDA-1088 or www.fda.gov/medwatch.

8 USE IN SPECIFIC POPULATIONS

- Pregnancy: Only use during pregnancy if the potential benefit justifies the potential risk to the fetus. (8.1)
- Lactation: Discontinue breast-feeding for up to 8 days after treatment. (8.2)
- Hepatic Impairment: Monitor patients longer for toxicity and drug interactions due to delayed clearance. (8.7)

FULL PRESCRIBING INFORMATION

WARNING: SEROTONIN SYNDROME WITH CONCOMITANT USE OF SEROTONERGIC DRUGS AND OPIOIDS

PROVAYBLUE may cause serious or fatal serotonergic syndrome when used in combination with serotonergic drugs and opioids. Avoid concomitant use of PROVAYBLUE with selective serotonin reuptake inhibitors (SSRIs), serotonin norepinephrine reuptake inhibitors (SNRIs), monoamine oxidase inhibitors (MAOIs) and opioids. [see Warnings and Precautions (5.1) and Drug Interactions (7.1)].

1 INDICATIONS AND USAGE

PROVAYBLUE is indicated for the treatment of pediatric and adult patients with acquired methemoglobinemia.

2 DOSAGE AND ADMINISTRATION

2.1 Dosage and Administration

- Ensure patent venous access prior to administration of PROVAYBLUE. Do not administer PROVAYBLUE subcutaneously.
- Administer PROVAYBLUE 1 mg/kg intravenously over 5-30 minutes.
- If the methemoglobin level remains greater than 30% or if clinical signs and symptoms persist, a repeat dose of PROVAYBLUE 1 mg/kg may be given one hour after the first dose.
- If methemoglobinemia does not resolve after 2 doses of PROVAYBLUE, consider initiating alternative interventions for treatment of methemoglobinemia.

2.2 Recommended Dosage for Renal Impairment

- The recommended dosage of PROVAYBLUE in patients with moderate or severe renal impairment (eGFR 15-59 mL/min/1.73 m^2) is a single dose of 1 mg/kg.
- If the methemoglobin level remains greater than 30% or if the clinical symptoms persist 1 hour after dosing, consider initiating alternative interventions for the treatment of methemoglobinemia.

2.3 Preparation

PROVAYBLUE is hypotonic and may be diluted before use in a solution of 50 mL 5% Dextrose Injection in order to avoid local pain, particularly in the pediatric population. Use the diluted solution immediately after preparation.

Avoid diluting with sodium chloride solutions, because it has been demonstrated that chloride reduces the solubility of methylene blue.

Parenteral drug products should be inspected visually for particulate matter and discoloration prior to administration, whenever solution and container permit.

Discard unused portion.

3 DOSAGE FORMS AND STRENGTHS

PROVAYBLUE (methylene blue) injection, USP: 50 mg/10 mL (5 mg/mL) or 10 mg/2 mL (5 mg/mL) clear dark blue solution in single-dose ampules or single-dose vials.

4 CONTRAINDICATIONS

PROVAYBLUE is contraindicated in the following conditions:

- Severe hypersensitivity reactions to methylene blue or any other thiazine dye [see Warnings and Precautions (5.2)].
- Patients with glucose-6-phosphate dehydrogenase deficiency (G6PD) due to the risk of hemolytic anemia [see Warnings and Precautions (5.3, 5.4)].

5 WARNINGS AND PRECAUTIONS

5.1 Serotonin Syndrome with Concomitant Use of Serotonergic Drugs and Opioids

The development of serotonin syndrome has been reported with the use of methylene blue class products. Most reports have been associated with concomitant use of serotonergic drugs (e.g., selective serotonin reuptake inhibitors (SSRIs), serotonin and norepinephrine reuptake inhibitors (SNRIs), monoamine oxidase inhibitors (MAOIs). Opioids and dextromethorphan may increase the risk of developing serotonin syndrome. Some of the reported cases were fatal. Symptoms associated with serotonin syndrome may include the following combination of signs and symptoms: mental status changes (e.g., agitation, hallucinations, delirium, and coma), autonomic instability (e.g., tachycardia, labile blood pressure, dizziness, diaphoresis, flushing, and hyperthermia), neuromuscular symptoms (e.g., tremor, rigidity, myoclonus, hyperreflexia, and incoordination), seizures, and/or gastrointestinal symptoms (e.g., nausea, vomiting, diarrhea). Avoid concomitant use of PROVAYBLUE with serotonergic drugs and opioids.

Patients treated with PROVAYBLUE should be monitored for the emergence of serotonin syndrome. If symptoms of serotonin syndrome occur, discontinue use of PROVAYBLUE, and initiate supportive treatment. Inform patients of the increased risk of serotonin syndrome and advise them to not to take serotonergic drugs within 72 hours after the last dose of PROVAYBLUE [see Drug Interactions (7), Patient Counseling Information (17)].

5.2 Hypersensitivity

Anaphylactic reactions to methylene blue class products have been reported. Patients treated with PROVAYBLUE should be monitored for anaphylaxis. If anaphylaxis or other severe hypersensitivity reactions (e.g., angioedema, urticaria, bronchospasm) should occur, discontinue use of PROVAYBLUE and initiate supportive treatment. PROVAYBLUE is contraindicated in patients who have experienced anaphylaxis or other severe hypersensitivity reactions to a methylene blue class product in the past.

5.3 Lack of Effectiveness

Methemoglobinemia may not resolve or may rebound after response to treatment with PROVAYBLUE in patients with methemoglobinemia due to aryl amines such as aniline or sulfa drugs such as dapsone. Monitor response to therapy with PROVAYBLUE through resolution of methemoglobinemia. If methemoglobinemia does not respond to 2 doses of PROVAYBLUE or if methemoglobinemia rebounds after a response, consider additional treatment options [see Dosage and Administration (2.2)].

Patients with glucose-6-phosphate dehydrogenase deficiency may not reduce PROVAYBLUE to its active form in vivo. PROVAYBLUE may not be effective in patients with glucose-6-phosphate dehydrogenase (G6PD) deficiency.

5.4 Hemolytic Anemia

Hemolysis can occur during treatment of methemoglobinemia with PROVAYBLUE. Laboratory testing may show Heinz bodies, elevated indirect bilirubin and low haptoglobin, but the Coombs test is negative. The onset of anemia may be delayed 1 or more days after treatment with PROVAYBLUE. The anemia may require red blood cell transfusions [see Adverse Reactions (6.1)]. Use the lowest effective number of doses of PROVAYBLUE to treat methemoglobinemia. Discontinue PROVAYBLUE and consider alternative treatments of methemoglobinemia if severe hemolysis occurs.

Treatment of patients with glucose-6-phosphate dehydrogenase (G6PD) deficiency with PROVAYBLUE may result in severe hemolysis and severe anemia. PROVAYBLUE is contraindicated for use in patients with glucose-6-phosphate dehydrogenase (G6PD) deficiency [see Contraindications (4)].

5.5 Interference with In Vivo Monitoring Devices

- Inaccurate Pulse Oximeter Readings

The presence of methylene blue in the blood may result in an underestimation of the oxygen saturation reading by pulse oximetry. If a measure of oxygen saturation is required during or shortly after infusion of PROVAYBLUE, it is advisable to obtain an arterial blood sample for testing by an alternative method.

- Bispectral index monitor

A fall in the Bispectral Index (BIS) has been reported following administration of methylene blue class products. If PROVAYBLUE is administered during surgery, alternative methods for assessing the depth of anesthesia should be employed.

5.6 Effects on Ability to Drive and Operate Machinery

Treatment with PROVAYBLUE may cause confusion, dizziness and disturbances in vision [see Adverse Reactions (6)]. Advise patients to refrain from driving or engaging in hazardous occupations or activities such as operating heavy or potentially dangerous machinery until such adverse reactions to PROVAYBLUE have resolved.

5.7 Interference with Laboratory Tests

PROVAYBLUE is a blue dye which passes freely into the urine and may interfere with the interpretation of any urine test which relies on a blue indicator, such as the dipstick test for leucocyte esterase.

6 ADVERSE REACTIONS

The following adverse reactions are discussed in greater detail in other sections of the labeling:

- Serotonin Syndrome with Concomitant Use of Serotonergic Drugs [see Warnings and Precautions (5.1)]
- Anaphylaxis [see Warnings and Precautions (5.2)]
- Lack of Effectiveness [see Warnings and Precautions (5.3)]
- Hemolytic Anemia [see Warnings and Precautions (5.4)]
- Interference with In-Vivo Monitoring Devices [see Warnings and Precautions (5.5)]
- Effects on Ability to Drive and Operate Machinery [see Warnings and Precautions (5.6)]
- Interference with Laboratory Tests [see Warnings and Precautions (5.7)]

6.1 Clinical Trials Experience

Because clinical trials are conducted under widely varying conditions, adverse reaction rates observed in the clinical trials of a drug cannot be directly compared to rates in the clinical trials of another drug and may not reflect the rates observed in practice.

The safety of PROVAYBLUE in adults with acquired methemoglobinemia was assessed in 31 patients who received at least 1 dose of PROVAYBLUE [see Clinical Studies (14)]. Most doses administered were 1 mg/kg (82.9%), but doses from 0.78 mg/kg to 2 mg/kg were administered. All patients received at least one dose of PROVAYBLUE; two received two doses, and one received three doses. Serious adverse reactions occurred in 3.2% of patients who received PROVAYBLUE. A serious adverse reaction of seizure-like phenomenon was reported in one patient. Adverse reactions (≥2%) included headache, hypokalemia, diarrhea, hypomagnesemia, myoclonus, nausea, and seizure-like phenomena.

The safety of PROVAYBLUE in pediatric patients with acquired methemoglobinemia was assessed in two retrospective case series that included two pediatric patients treated with PROVAYBLUE and 12 treated with another methylene blue product. The case series included patients in the following age groups: 3 neonates (<1 month), 4 infants (1 month to <2 years), 4 children (2 years to <12 years), and 3 adolescents (12 years to <17 years). The safety profile in pediatric patients was similar to that in adult patients.

Other adverse reactions reported to occur following the administration of methylene blue class products include the following:

Blood and lymphatic system disorders: hemolytic anemia, hemolysis, hyperbilirubinemia

Cardiac disorders: palpitations, tachycardia

Eye disorders: eye pruritus, ocular hyperemia, vision blurred

Gastrointestinal disorders: abdominal pain lower, dry mouth, flatulence, glossodynia, tongue eruption

General disorders and administration site conditions: death, infusion site extravasation, infusion site induration, infusion site pruritus, infusion site swelling, infusion site urticaria, peripheral swelling, thirst

Investigations: elevated liver enzymes

Musculoskeletal and connective tissue disorders: myalgia

Renal and urinary disorders: dysuria

Respiratory, thoracic and mediastinal disorders: nasal congestion, oropharyngeal pain, rhinorrhea, sneezing

Skin and subcutaneous tissue disorders: necrotic ulcer, papule, phototoxicity

Vascular disorders: hypertension

7 DRUG INTERACTIONS

Clinically significant drug interactions with PROVAYBLUE are described below:
The concomitant use of PROVAYBLUE with other drugs that affect the serotonergic neurotransmitter system has resulted in serotonin syndrome. Although the mechanism is not clearly understood, literature reports suggest PROVAYBLUE is a potent reversible inhibitor of monoamine oxidase. Avoid concomitant use of PROVAYBLUE with medicinal products that enhance serotonergic transmission including antidepressants like SSRIs (selective serotonin reuptake inhibitors), SNRIs (serotonin and norepinephrine reuptake inhibitors), MAOIs (monoamine oxidase inhibitors), bupropion, buspirone, clomipramine, mirtazapine, linezolid, opioids, and dextromethorphan because of the potential for serious CNS reactions, including potentially fatal serotonin syndrome. If the intravenous use of PROVAYBLUE cannot be avoided in patients treated with serotonergic medicinal products, choose the lowest possible dose and observe the patient closely for CNS effects for up to 4 hours after administration [see Warning and Precautions (5.1) and Clinical Pharmacology (12.3)].

8 USE IN SPECIFIC POPULATIONS

8.1 Pregnancy

Risk Summary

PROVAYBLUE may cause fetal harm when administered to a pregnant woman. Intra-amniotic injection of pregnant women with a methylene blue class product during the second trimester was associated with neonatal intestinal atresia and fetal death. Methylene blue produced adverse developmental outcomes in rats and rabbits when administered orally during organogenesis at doses at least 32 and 16 times, respectively, the clinical dose of 1 mg/kg (see Data). Advise pregnant women of the potential risk to a fetus.

In the U.S. general population, the estimated background risks of major birth defects and miscarriage in clinically recognized pregnancies are 2-4% and 15-20%, respectively.

Clinical Considerations

Fetal/neonatal adverse reactions

Intra-amniotic injection of a methylene blue class product hours to days prior to birth can result hyperbilirubinemia, hemolytic anemia, skin staining, methemoglobinemia, respiratory distress and photosensitivity in the newborn. Following administration of PROVAYBLUE to a pregnant woman at term, observe the newborn for these adverse reactions and institute supportive care.

Data

Animal Data

Methylene blue was administered orally to pregnant rats at doses of 50 to 350 mg/kg/day, during the period of organogenesis. Maternal and embryofetal toxicities were observed at all doses of methylene blue and were most evident at the 200 and 350 mg/kg/day doses. Maternal toxicity consisted of increased spleen weight. Embryo-fetal toxicities included reduced fetal weight, post-implantation loss, edema, and malformations including enlarged lateral ventricles. The dose of 200 mg/kg (1200 mg/m^2) in rats is approximately 32 times a clinical dose of 1 mg/kg based on body surface area.

Methylene blue was administered orally to pregnant rabbits at doses of 50, 100, or 150 mg/kg/day, during the period of organogenesis. Maternal death was observed at the methylene blue dose of 100 mg/kg. Embryofetal toxicities included spontaneous abortion at all dose levels and a malformation (umbilical hernia) at the 100 and 150 mg/kg/day doses. The dose of 50 mg/kg (600 mg/m^2) in rabbits is approximately 16 times a clinical dose of 1 mg/kg based on body surface area.

8.2 Lactation

Risk Summary

There is no information regarding the presence of methylene blue in human milk, the effects on the breastfed infant, or the effects on milk production. Because of the potential for serious adverse reactions including genotoxicity, discontinue breast-feeding during and for up to 8 days after treatment with PROVAYBLUE [see Clinical Pharmacology (12.3)].

8.4 Pediatric Use

The safety and effectiveness of PROVAYBLUE for the treatment of acquired methemoglobinemia have been established in pediatric patients. Use of PROVAYBLUE is supported by two retrospective case series that included 2 pediatric patients treated with PROVAYBLUE and 12 treated with another methylene blue class product. The case series included pediatric patients in the following age groups: 3 neonates (less than 1 month), 4 infants (1 month up to less than 2 years), 4 children (2 years up to less than 12 years), and 3 adolescents (12 years to less than 17 years). The efficacy outcomes were consistent across pediatric and adult patients in both case series [see Clinical Studies (14)].

8.5 Geriatric Use

Clinical studies of PROVAYBLUE did not include sufficient numbers of subjects aged 65 and over to determine whether they respond differently from younger subjects. Other reported clinical experience has not identified differences in responses between the elderly and younger patients. PROVAYBLUE is known to be substantially excreted by the kidney, so the risk of adverse reactions to this drug may be greater in patients with impaired renal function. Because elderly patients are more likely to have decreased renal function, treatment of methemoglobinemia in these patients should use the lowest number of doses needed to achieve a response [see Dosage and Administration (2)].

8.6 Renal Impairment

Methylene blue concentrations increased in subjects with renal impairment (eGFR 15 to 89 mL/min/1.73m^2) significantly [see Clinical Pharmacology (12.3)]. Adjust PROVAYBLUE dosage in patients with moderate or severe renal impairment (eGFR 15 to 59 mL/min/1.73 m^2) [see Dosage and Administration (2.2)]. No dose adjustment is recommended in patients with mild renal impairment (eGFR 60 – 89 mL/min/1.73 m^2).

8.7 Hepatic Impairment

Methylene blue is extensively metabolized in the liver. Monitor patients with any hepatic impairment for toxicities and potential drug interactions for an extended period of time following treatment with PROVAYBLUE.

10 OVERDOSAGE

Hypotension, wheezing and reduced oxygenation have been reported in patients who received methylene blue class products in single doses of 3 mg/kg or more.

Administration of large intravenous doses (cumulative dose ≥ 7 mg/kg) of a methylene blue class product caused nausea, vomiting, precordial pain, dyspnea, tachypnea, chest tightness, tachycardia, apprehension, tremor, mydriasis, blue staining of the urine, the skin and mucous membranes, abdominal pain, dizziness, paresthesia, headache, confusion, mild methemoglobinemia (up to 7%) and electrocardiogram changes (T-wave flattening or inversion). These effects lasted 2-12 hours following administration.

A severe overdosage (single dose of 20 mg/kg or more) of a methylene blue class product caused severe intravascular hemolysis, hyperbilirubinemia and death.

In case of overdose of PROVAYBLUE, maintain the patient under observation until signs and symptoms have resolved, monitor for cardiopulmonary, hematologic and neurologic toxicities, and institute supportive measures as necessary.

11 DESCRIPTION

Methylene blue is an oxidation-reduction agent.

Its chemical name is 3,7-bis(dimethylamino)phenothiazin-5-ium, chloride hydrate. The molecular formula of methylene blue is C16H18ClN3S.xH2O and its molecular weight of 319.86 g/mol for the anhydrous form. The structural formula of methylene blue is:

PROVAYBLUE (methylene blue) injection USP is a sterile solution intended for intravenous administration. Each mL of solution contains 5 mg methylene blue and water for injection. PROVAYBLUE (methylene blue) injection, USP: is a clear dark blue solution with a pH value between 3.0 and 4.5. The osmolality is between 10 and 15 mOsm/kg. PROVAYBLUE (methylene blue) injection strength is expressed in terms of trihydrate.

12 CLINICAL PHARMACOLOGY

12.1 Mechanism of Action

Methylene blue is a water soluble thiazine dye that promotes a non-enyzmatic redox conversion of metHb to hemoglobin. In situ, methylene blue is first converted to leucomethylene blue (LMB) via NADPH reductase. It is the LMB molecule which then reduces the ferric iron of metHb to the ferrous state of normal hemoglobin.

12.2 Pharmacodynamics

Low concentrations of methylene blue speeds up the in vivo conversion of methemoglobin to hemoglobin. Methylene blue has been observed to stain tissues selectively. The exposure-response or –safety relationship for methylene is unknown.

Cardiac Electrophysiology

The results of a thorough QT study demonstrated PROVAYBLUE at an intravenous dose of 2 mg/kg as a 5-minute intravenous infusion had no effect on the QT, PR or QRS intervals.

12.3 Pharmacokinetics

The mean (CV%) Cmax and AUC of methylene blue 2,917 ng/mL (39%) and 13977 ng.hr/mL (21%) following a 2 mg/kg dose administered as a 5-minute intravenous infusion.

Distribution

The mean± standard deviation steady state volume of distribution of a 2 mg/kg dose of PROVAYBLUE was 255 L ± 58. The mean plasma protein binding of methylene blue is approximately 94% in vitro. Methylene blue exhibits concentration-dependent partitioning into blood cells in vitro. The blood-to-plasma ratio was 5.1±2.8 at 5 minutes from the start of a 2 mg/kg dose administered as a 5-minute intravenous infusion and reached a plateau of 0.6 at 4 hours in a clinical study. Methylene Blue is a substrate for the P-glycoprotein (P-gp, ABCB1) transporter, but not for BCRP or OCT2 in vitro.

Elimination

Methylene blue has a half-life of approximately 24 hours in humans.

Metabolism

Methylene blue is metabolized by CYPs 1A2, 2C19 and 2D6 in vitro; however, the predominant in vitro pathway appears to be UGT-mediated conjugation by multiple UGT enzymes, including UGT1A4 and UGT1A9.

Azure B, which is a minor impurity in methylene blue, is also formed in humans as a metabolite of methylene blue, with an overall drug/metabolite AUC ratio of greater than 6:1. Azure B has 8-fold lower potency than methylene blue.

Excretion

Approximately 40% of methylene blue is excreted into the urine unchanged.

Specific Populations

Renal Impairment

After a single 1 mg/kg dose of PROVAYBLUE, AUC0-96h increased by 52%, 116%, and 192% in subjects with mild (estimated glomerular filtration rate (eGFR) 60 – 89 mL/min/1.73 m^2), moderate (eGFR 30-59 mL/min/1.73m^2), and severe (eGFR 15-29 mL/min/1.732m^2) renal impairment, respectively. Cmax increased by 42%, 34%, and 15% in subjects with mild, moderate, and severe renal impairment respectively [see Dosage and Administration (2.2) and Use in Specific Populations (8.6)]. The half-life was unchanged in patients with mild to moderate renal impairment.

The AUC0-96h of Azure B after a single 1 mg/kg dose increased by 29%, 94%, and 339% in subjects with mild (estimated glomerular filtration rate (eGFR) 60 – 89 mL/min/1.73 m^2), moderate (eGFR 30-59 mL/min/1.73m^2), and severe (eGFR 15-29 mL/min/1.732m^2) renal impairment, respectively. Cmax increased by 23%, 13%, and 65% in subjects with mild, moderate, and severe renal impairment, respectively [see Dosage and Administration (2.2) and Use in Specific Populations (8.6)]

Drug Interactions Studies

Clinical Studies:

The coadministration of 2 mg/kg dose of PROVAYBLUE with midazolam (a CYP3A4 substrate), caffeine (a CYP1A2 substrate), warfarin (a CYP2C9 substrate), and dextromethorphan (a CYP2D6 substrate) in a cocktail study did not affect the exposure of these substrates compared to their exposure without PROVAYBLUE administration.

In Vitro Studies:

Cytochrome P450 (CYP450) Enzymes:

Methylene blue inhibits CYP isozymes 1A2, 2B6, 2C8, 2C9, 2C19, 2D6 and 3A4/5. Possible time-dependent inhibition of CYP2C9, CYP2D6 and CYP3A4/5 (testosterone as substrate) was also observed. Methylene blue induces CYP1A2 but does not induce CYP2B6 or CYP3A4.

UDP-Glucuronosyltransferase (UGT):

Methylene blue inhibits UGT1A9 and UGT1A4, but did not significantly inhibit UGTs 1A1, 1A3, 1A6, 2B7 or 2B15.

Transporter:

Methylene blue is both a substrate for and an inhibitor of P-gp but is not a substrate for BCRP or OCT2 in vitro. Methylene blue is not a significant inhibitor of BCRP, OAT1, OAT3, OAT1B1 or OAT1B3. Methylene blue inhibits OCT2, MATE1 and MATE2-K.

13 NONCLINICAL TOXICOLOGY

13.1 Carcinogenesis, Mutagenesis, Impairment of Fertility

In a two-year carcinogenicity study, rats were administered oral doses of methylene blue at 5, 25, or 50 mg/kg. Methylene blue caused pancreatic islet adenomas or carcinomas (combined) in male rats. In a two-year carcinogenicity study, mice were administered oral doses of methylene blue at 2.5, 12.5, or 25 mg/kg. There were no drug-related neoplastic findings in mice.

Methylene blue was genotoxic in gene mutation assays in bacteria (Ames test), and in an in vitro sister chromatid exchange test and an in vitro chromosomal aberration test in Chinese hamster ovary (CHO) cells. Methylene blue was negative for micronucleus induction in bone marrow or peripheral blood collected from mice treated with methylene blue.

Fertility studies with methylene blue have not been conducted. In vitro, methylene blue reduced motility of human sperm in a concentration dependent manner.

14 CLINICAL STUDIES

14.1 Treatment of Acquired Methemoglobinemia

The efficacy of PROVAYBLUE in the treatment of patients with methemoglobinemia was evaluated in 31 adult patients with acquired methemoglobinemia across two studies: NCT03395223, a prospective, interventional, open-label, single-arm study, and NCT03542760, a prospective, multicenter, observational registry. Of the 31 subjects enrolled 90% were white, 10% were black, 58% were female, and 42% were male. Hispanic or Latino was 9.7%; non-Hispanic or Latino was 67.7%, and ethnicity data were missing for 22.6%. The mean age was 45.6 years, and the ages ranged from 19 to 72 years. Each individual received at least 1 intravenous dose of PROVAYBLUE; two received 2 doses and one received 3 doses. Most doses administered were 1 mg/kg (82.9%), but doses from 0.78 mg/kg to 2 mg/kg were administered. The recommended PROVAYBLUE dose is 1 mg/kg; lower or greater doses are not recommended. The maximum recommended number of doses is two , a prospective, interventional, open-label, single-arm study, and NCT03542760, a prospective, multicenter, observational registry. Of the 31 subjects enrolled 90% were white, 10% were black, 58% were female, and 42% were male. Hispanic or Latino was 9.7%; non-Hispanic or Latino was 67.7%, and ethnicity data were missing for 22.6%. The mean age was 45.6 years, and the ages ranged from 19 to 72 years. Each individual received at least 1 intravenous dose of PROVAYBLUE; two received 2 doses and one received 3 doses. Most doses administered were 1 mg/kg (82.9%), but doses from 0.78 mg/kg to 2 mg/kg were administered. The recommended PROVAYBLUE dose is 1 mg/kg; lower or greater doses are not recommended. The maximum recommended number of doses is two [see Dosage and Administration (2.1)].

In total, 29 of the 31 (93.5%) subjects had post treatment methemoglobin (metHb) assessment; 28 of the 29 subjects had baseline metHb with a mean concentration of 18.4% and a range of 4.1% to 74.4%. Twenty-six of the 28 (92.9%) subjects who had baseline metHb had at least a 50% reduction in metHB from baseline in their first assessment post baseline. This first post dosing assessment occurred from 0.2 to 27.3 hours from the end of first PROVAYBLUE infusion with a median time of 2.7 hours. There were 12 subjects that had baseline metHb and had metHb assessed within 2 hours of the end of the first PROVAYBLUE treatment; 9 of the 12 (75%; 95% CI (42.8%,93.3%)) had at least a 50% reduction in metHb at 1 hour postdosing.

Available vital sign data including blood pressure, heart rate and respiratory rate were reviewed at baseline and compared to data collected within 2 hours post PROVAYBLUE infusion. Prior to treatment with PROVAYBLUE, 16 of the 23 (70%) of patients had a respiratory rate exceeding the upper limit of normal (≥ 20 bpm). Of these, 10 of the 16 (63%) experienced a normalization of respiratory rate within 2 hours post ProvayBlue infusion. There was minimal impact on other vital signs.

At baseline, the most common prespecified signs and symptoms of methemoglobinemia (reported by ≥2 subjects [6.5%] overall) were cyanosis (32.3%), dyspnea (25.8%), fatigue (25.8%), depressed CNS (9.7%), headache (6.5%), weakness (6.5%), and dizziness (6.5%). Following treatment with PROVAYBLUE, signs and symptoms of methemoglobinemia improved.

The efficacy of PROVAYBLUE in the treatment of methemoglobinemia in pediatric patients was assessed in 14 patients in two retrospective case series (2 patients received PROVAYBLUE and 12 who received another methylene blue product). The ages ranged from 6 days to 16 years. The efficacy outcomes were consistent across the pediatric and adult populations.

16 HOW SUPPLIED/STORAGE AND HANDLING

PROVAYBLUE (methylene blue) injection, USP: is supplied in 10 mL and 2 mL single-dose ampules or single-dose vials. Each 10 mL ampule and vial contains 50 mg of methylene blue as a clear dark blue solution. Each 2 mL ampule and vial contains 10 mg of methylene blue as a clear dark blue solution. A box contains five ampules or vials.

Box of 5 ampules of 50 mg/10 mL: NDC 0517-0374-05

Box of 5 ampules of 10 mg/2 mL: NDC 0517-0125-05

Box of 5 vials of 50 mg/10 mL: NDC 0517-0381-05

Box of 5 vials of 10 mg/2 mL: NDC 0517-0371-05

Storage:

Store at 20°C to 25°C (68°F to 77°F); excursions permitted to 15°C to 30°C (59°F to 86°F). [See USP Controlled Room Temperature]

Any unused product or waste material should be disposed of in accordance with local practice.

Do not refrigerate or freeze.

Keep the ampule or the vial in the original package to protect from light.

17 PATIENT COUNSELING INFORMATION

Serotonin Syndrome

Advise patients of the possibility of serotonin syndrome, especially with concomitant use of serotonergic agents such as medications to treat depression and migraines. Advise patients to seek immediate medical attention if the following symptoms occur after treatment with PROVAYBLUE: changes in mental status, autonomic instability, or neuromuscular symptoms with or without gastrointestinal symptoms [see Warnings and Precautions (5.1)].

Pregnancy

Advise pregnant women of the potential risk to the fetus with the use of PROVAYBLUE during pregnancy [see Use in Specific populations (8.1)].

Breastfeeding

Advise patients to discontinue breast-feeding for up to 8 days after treatment with PROVAYBLUE [see Use in Specific populations (8.2)].

Driving and Using Machines

Advise patients to avoid driving and use of machines during treatment with PROVAYBLUE. Driving can be affected as a result of a confusional state, dizziness and possible eye disturbances [see Warnings and Precautions (5.6)].

Phototoxicity

Advise patients to take protective measures against exposure to light, because phototoxicity may occur after administration of methylene blue [see Adverse Reactions (6.1)].

Skin and Body Fluid Blue Discoloration

Advise patients that PROVAYBLUE may cause a blue discoloration of the skin and body fluids [see Adverse Reactions (6.1)].

Manufactured for:
PROVEPHARM SAS
22 rue Marc Donadille
13013 Marseille, France

Ampules manufactured by:

CENEXI
52 rue Marcel et Jacques Gaucher
94120 Fontenay sous Bois, France

Vials manufactured by: CENEXI HSC
2 rue Louis Pasteur
14200 Hérouville-Saint-Clair, France

Distributed by:
American Regent, Inc.
Shirley, NY 11967
Questions? : 1-800-734-9236

Principal Display Panel - 50 mg/10 mL (5 mg/mL) Ampule Label

NDC 0517-0374-01 Rx Only

ProvayBlue®
(methylene blue) Injection USP

50 mg/10 mL
(5 mg/mL) (0.5%)

Intravenous use only

Use 5% Dextrose Injection When Diluting

Single-Dose Ampule
Discard Unused Portion

Manufactured by Cenexi for:
Provepharm SAS

Distributed by:
American Regent, INC.
Shirley, NY 11967

Principal Display Panel - 50 mg/10 mL (5 mg/mL) Carton Label

Rx only

NDC 0517-0374-05

ProvayBlue®

(methylene blue)
Injection USP

5 Single-Dose Ampules.
Discard Unused Portion

50 mg/10 mL (5 mg/mL) (0.5%)

Intravenous use only

For slow intravenous injection

Use 5% Dextrose Injection When Diluting

Distributed by:

AMERICAN REGENT

PROVEPHARM

Principal Display Panel - 10 mg/2 mL (5 mg/mL) Ampule Label

NDC 0517-0125-01 Rx Only

ProvayBlue®
(methylene blue) Injection USP

10 mg/2 mL
(5 mg/mL) (0.5%)

Intravenous use only

Use 5% Dextrose Injection When Diluting

Single Dose Ampule
Discard Unused Portion

Manufactured by Cenexi for:
Provepharm SAS

Distributed by:
American Regent, INC.
Shirley, NY 11967

Principal Display Panel - 10 mg/2 mL (5 mg/mL) Carton Label

Rx only

NDC 0517-0125-05

ProvayBlue®

(methylene blue)
Injection USP

5 Single-Dose Ampules.
Discard Unused Portion

10 mg/2 mL (5 mg/mL) (0.5%)

Intravenous use only

For slow intravenous injection

Use 5% Dextrose Injection When Diluting

Distributed by:

AMERICAN REGENT

PROVEPHARM

Principal Display Panel - 50 mg/10 mL (5 mg/mL) Single-Dose Vial Label

NDC 0517-0381-01

ProvayBlue®

(methylene blue) Injection USP

50 mg/10 mL (5 mg/mL) (0.5%)

Rx only

Intravenous use only

Use 5% Dextrose Injection When Diluting

Single-Dose Vial
Discard Unused Portion

Manufactured by Cenexi for:
Provepharm SAS

Distributed by:
American Regent, Inc.
Shirley, NY 11967

Principal Display Panel - 50 mg/10 mL (5 mg/mL) Single-Dose Vial Carton Label

NDC 0517-0381-05

ProvayBlue®

(methylene blue) Injection USP

50 mg/10 mL (5 mg/mL) (0.5%)

5 Single-Dose Vials

Discard Unused Portion

Intravenous use only

For slow intravenous injection

Use 5% Dextrose Injection When Diluting

Distributed by:
AMERICAN REGENT

PROVEPHARM

Principal Display Panel - 10 mg/2 mL (5 mg/mL) Single-Dose Vial Label

NDC 0517-0371-01

ProvayBlue®

(methylene blue) Injection USP

10 mg/2 mL (5 mg/mL) (0.5%)

Rx only

Intravenous use only

Use 5% Dextrose Injection When Diluting

Single-Dose Vial.
Discard Unused Portion

Manufactured by Cenexi for:
Provepharm SAS

Distributed by:
American Regent, Inc.
Shirley, NY 11967

Principal Display Panel - 10 mg/2 mL (5 mg/mL) Single-Dose Vial Carton Label

Rx only

NDC 0517-0371-05

ProvayBlue®

(methylene blue)
Injection USP

10 mg/2 mL (5 mg/mL) (0.5%)

5 Single-Dose Vials

Discard Unused Portion

Intravenous use only

For slow intravenous injection

Use 5% Dextrose Injection When Diluting

Distributed by:
AMERICAN REGENT

PROVEPHARM